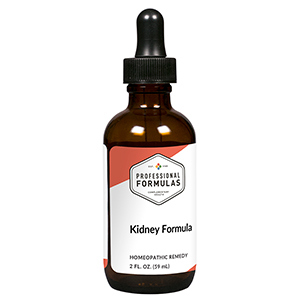 DRUG LABEL: Kidney Formula
NDC: 63083-2107 | Form: LIQUID
Manufacturer: Professional Complementary Health Formulas
Category: homeopathic | Type: HUMAN OTC DRUG LABEL
Date: 20190815

ACTIVE INGREDIENTS: TSAO-T 2 [hp_X]/59 mL; LYGODIUM JAPONICUM SPORE 2 [hp_X]/59 mL; IMPERATA CYLINDRICA ROOT 2 [hp_X]/59 mL; CIRSIUM ARVENSE STEM 2 [hp_X]/59 mL; LOBELIA INFLATA WHOLE 3 [hp_X]/59 mL
INACTIVE INGREDIENTS: ALCOHOL; WATER

C107

ACTIVE INGREDIENTS

Chin-Chien-Tsao 2X
Hai-Chin Sha 2X
Mao-Gen 2X
Xiao-Ji 2X
Pan-Pien-Lien 3X

QUESTIONS

Professional Formulas

PO Box 2034 Lake Oswego, OR 97035

INDICATIONS

For the temporary relief of minor nausea, changes in appetite, fatigue, disturbed sleep, muscle twitches, or cramps.*

PURPOSE

*Claims based on traditional homeopathic practice, not accepted medical evidence. Not FDA evaluated.

WARNINGS

Severe or persistent symptoms may be serious. Consult a doctor promptly. Keep out of the reach of children. In case of overdose, get medical help or contact a poison control center right away. If pregnant or breastfeeding, ask a healthcare professional before use.

Keep out of the reach of children.

PREGNANCY OR BREAST FEEDING

If pregnant or breastfeeding, ask a healthcare professional before use.

DIRECTIONS

Place drops under tongue 30 minutes before/after meals. Adults and children 12 years and over: Take 10 drops up to 3 times per day. Consult a physician for use in children under 12 years of age.

OTHER INFORMATION

Tamper resistant. If seal is broken, do not use. After opening, close container tightly and store at room temperature away from heat.

INACTIVE INGREDIENTS

20% ethanol, purified water.

LABEL

Est 1985

Professional Formulas

Complementary Health

Kidney Formula

Homeopathic Remedy

2 FL. OZ. (59 mL)